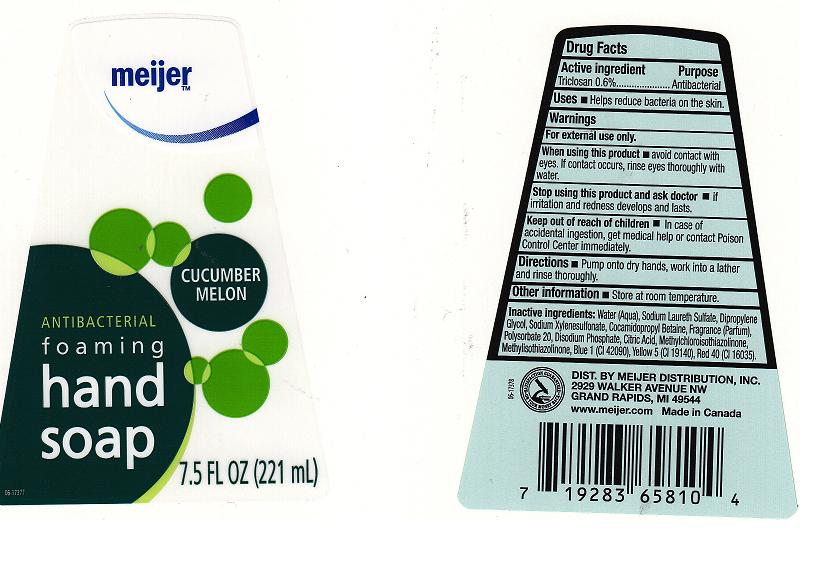 DRUG LABEL: ANTIBACTERIAL FOAMING
NDC: 41250-187 | Form: LIQUID
Manufacturer: MEIJER DISTRIBUTION INC
Category: otc | Type: HUMAN OTC DRUG LABEL
Date: 20111116

ACTIVE INGREDIENTS: TRICLOSAN 0.6 mL/100 mL
INACTIVE INGREDIENTS: WATER; SODIUM LAURETH SULFATE; DIPROPYLENE GLYCOL; SODIUM XYLENESULFONATE; COCAMIDOPROPYL BETAINE; POLYSORBATE 20; SODIUM PHOSPHATE; CITRIC ACID MONOHYDRATE; METHYLCHLOROISOTHIAZOLINONE; METHYLISOTHIAZOLINONE

DRUG FACTS

ACTIVE INGREDIENT

TRICLOSAN 0.6%

PURPOSE

ANTIBACTERIAL

USES

HELPS REDUCE BACTERIA ON THE SYSTEM

WARNINGS

FOR EXTERNAL USE ONLY

WHEN USING THIS PRODUCT

AVOID CONTACT WITH EYES. IF CONTACT OCCURS, RINSE EYES THOROUGHLY WITH WATER.

STOP USING THIS PRODUCT AND ASK DOCTOR

IF IRRITATION AND REDNESS DEVELOP AND LAST

KEEP OUT OF REACH OF CHILDREN

IN CASE OF ACCIDENTAL INGESTION, GET MEDICAL HELP OR CONTACT POISON CONTROL CENTER IMMEDIATELY.

DIRECTIONS

PUMP ONTO DRY HANDS, WORK INTO A LATHER AND RINSE THOROUGHLY.

OTHER INFORMATION

STORE AT ROOM TEMPERATURE

INACTIVE INGREDIENTS

WATER (AQUA), SODIUM LAURETH SULFATE, DIPROPYLENE GLYCOL, SODIUM XYLENESULFONATE, COCAMIDOPROPYL BETAINE, FRAGRANCE (PARFUM), POLYSORBATE 20, DISODIUM PHOSPHATE, CITRIC ACID, METHYLISOTHIAZOLINOE, METHYLISOTHIAZOLINONE, BLUE 1 (CI 42090), YELLOW 5 (CI 19140), RED 40 (CI 16035)